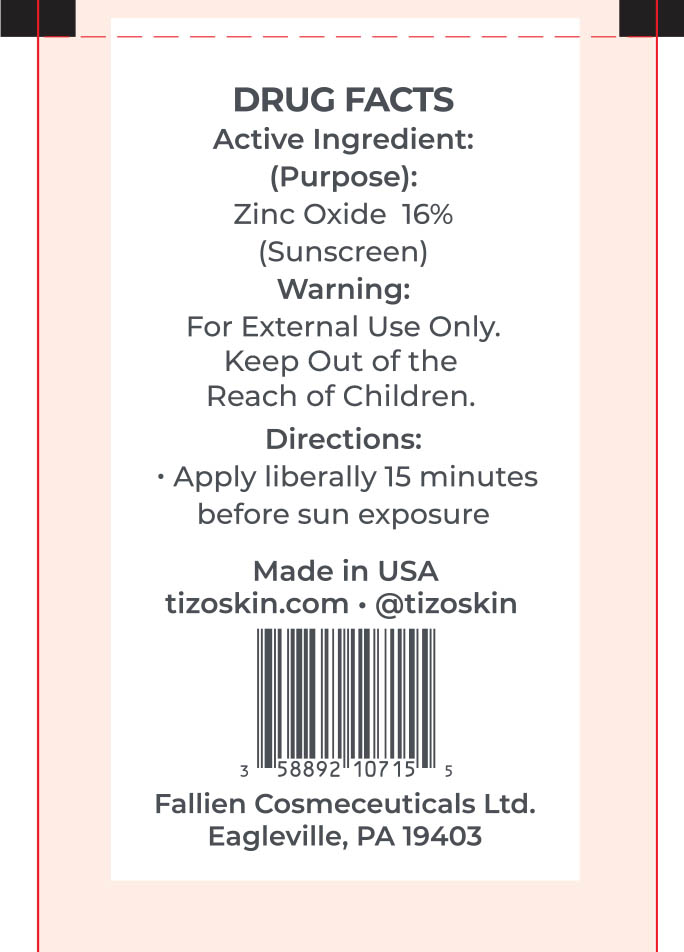 DRUG LABEL: TiZO Photoceutical AM Replenish Non-Tinted
NDC: 58892-107 | Form: CREAM
Manufacturer: Fallien Cosmeceuticals, LTD
Category: otc | Type: HUMAN OTC DRUG LABEL
Date: 20250127

ACTIVE INGREDIENTS: ZINC OXIDE 160 mg/1 g
INACTIVE INGREDIENTS: POLYHYDROXYSTEARIC ACID (2300 MW); ALPHA-TOCOPHEROL ACETATE; DIMETHICONE CROSSPOLYMER; DIMETHICONE/VINYL DIMETHICONE CROSSPOLYMER (SOFT PARTICLE); CAPRYLIC/CAPRIC TRIGLYCERIDE; CERAMIDE 3; CYCLOPENTASILOXANE; HYDROGEN DIMETHICONE (20 CST); TETRAHEXYLDECYL ASCORBATE; VINYL DIMETHICONE/METHICONE SILSESQUIOXANE CROSSPOLYMER; CYCLOHEXASILOXANE; PEG-10 DIMETHICONE (600 CST); DIMETHICONOL (2000 CST); DIMETHICONE

Active Ingredient:

Zinc Oxide 16%

(Purpose)

Sunscreen

Directions:

Apply liberally 15 minutes before sun exposure.

Warning:

For external use only.

Warning and Directions:

For external use only. Apply liberally 15 minutes before sun exposure.

Warning:

Kepp Out of the Reach of Children.

INACTIVE INGREDIENT

Capric/Caprylic Triglyceride, Ceramide 3, Cyclohexasiloxane, Cyclopentasiloxane, Dimethicone, Dimethicone Crosspolymer, Dimethicone/Vinyl Dimethicone Crosspolymer, Dimethiconol, Hydrogen Dimethicone, PEG-10 Dimethicone, Polyhydroxystearic Acid, Tetrahexyldecyl Ascorbate, Tocopheryl Acetate, Vinyl Dimethicone/Methicone Silsesquioxane Crosspolymer